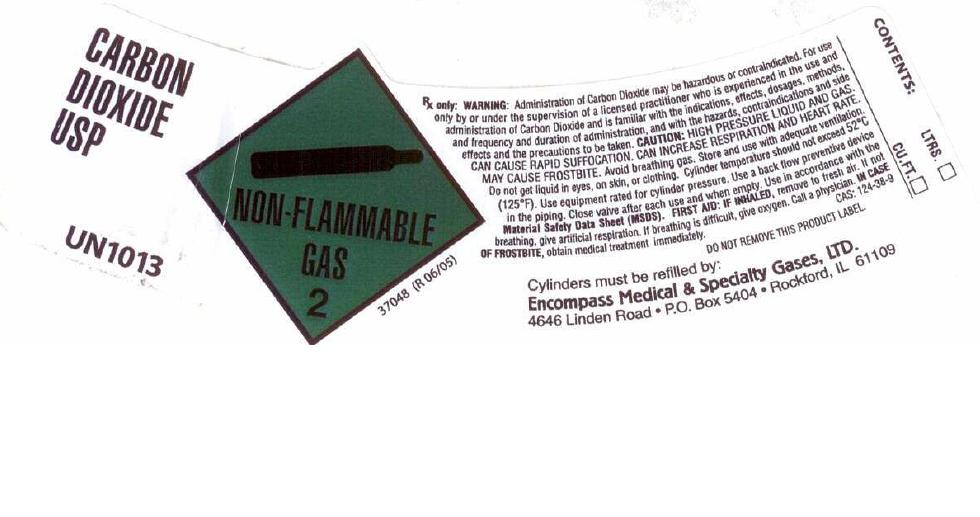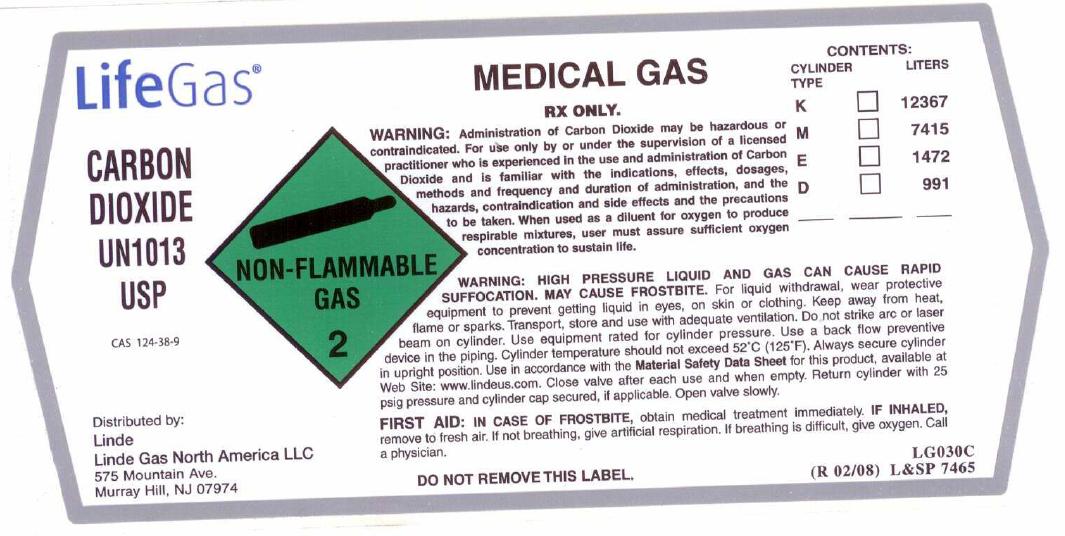 DRUG LABEL: Carbon Dioxide
NDC: 48883-003 | Form: GAS
Manufacturer: Encompass Medical & Specialty Gases, Ltd.
Category: prescription | Type: HUMAN PRESCRIPTION DRUG LABEL
Date: 20101203

ACTIVE INGREDIENTS: Carbon Dioxide 990 mL/1 L

Carbon Dioxide Label

PACKAGE LABEL

CARBON DIOXIDE USP UN1013
NON-FLAMMABLE GAS 2 37048 (R 06/05)
Rx only. WARNING: Administration of Carbon Dioxide may be hazardous or contraindicated. For use only by or under supervision of a licensed practitioner who is experienced in the use and administration of Carbon Dioxide and is familiar with the indications, effects, dosages, methods, and frequency and duration of administration, and with the hazards, contraindications, and side effects and the precautions to be taken. CAUTION: HIGH PRESSURE LIQUID AND GAS. CAN CAUSE RAPID SUFFOCATION. CAN INCREASE RESPIRATION AND HEART RATE. MAY CAUSE FROSTBITE. Avoid breathing gas. Store and use with adequate ventilation. Do not get liquid in eyes, on skin, and clothing. Cylinder temperatures should not exceed 52C (125F). Use equipment rated for cylinder pressure. Use a back flow preventive device in the piping. Close valve after each use and when empty. Use in accordance with the Material Safety Data Sheet (MSDS). FIRST AID: IF INHALED, remove to fresh air. If not breathing, give artificial respiration. If breathing is difficult, give oxygen. Call a physician. IN CASE OF FROSTBITE, obtain medical treatment immediately. CAS: 124-38-9
DO NOT REMOVE THIS PRODUCT LABEL.
Cylinders must be refilled by:
Encompass Medical and Specialty Gases, LTD. 4646 Linden Road P.O. Box 5404 Rockford, IL 61109
CONTENTS: LTRS CU. FT.

PACKAGE LABEL

LifeGas
CARBON DIOXIDE UN1013 USP
CAS: 124-38-9
Distributed by: Linde Linde Gas North America LLC 575 Mountain Ave. Murray Hill, NJ 07974
NON-FLAMMABLE GAS 2
MEDICAL GAS
Rx only. WARNING: Administration of Carbon Dioxide may be hazardous or contraindicated. For use only by or under supervision of a licensed practitioner who is experienced in the use and administration of Carbon Dioxide and is familiar with the indications, effects, dosages, methods, and frequency and duration of administration, and with the hazards, contraindications, and side effects and the precautions to be taken. When used as a diluent for oxygen to produce respirable mixtures, user must assure sufficient oxygen concentration to sustain life.
WARNING: HIGH PRESSURE LIQUID AND GAS. CAN CAUSE RAPID SUFFOCATION. MAY CAUSE FROSTBITE. For liquid withdrawal, wear protective equipment to prevent getting liquid in eyes, on skin, or clothing. Keep away from heat, flame or sparks. Transport, store and use with adequate ventilation. Do not strike arc or laser beam on cylinder. Use equipment rated for cylinder pressure. Use a back flow preventive device in the piping. Cylinder temperatures should not exceed 52C (125F). Always secure cylinder in upright position. Use in accordance with the Material Safety Data Sheet for this product, available at Web Site: www.lindeus.com. Close valve after each use and when empty. Return cylinder with 25 psig pressure and cylinder cap secured, if applicable. Open valve slowly. FIRST AID: IN CASE OF FROSTBITE, obtain medical treatment immediately. IF INHALED, remove to fresh air. If not breathing, give artificial respiration. If breathing is difficult, give oxygen. Call a physician.
DO NOT REMOVE THIS LABEL.
LG030C (R 02/08) L and SP 7465
CONTENTS: CYLINDER TYPE K M E D
LITERS 12367 7415 1472 991